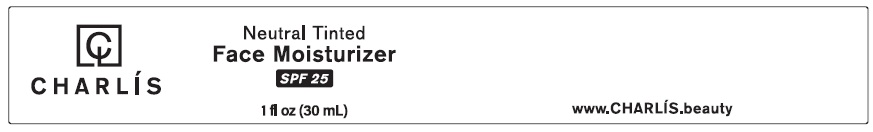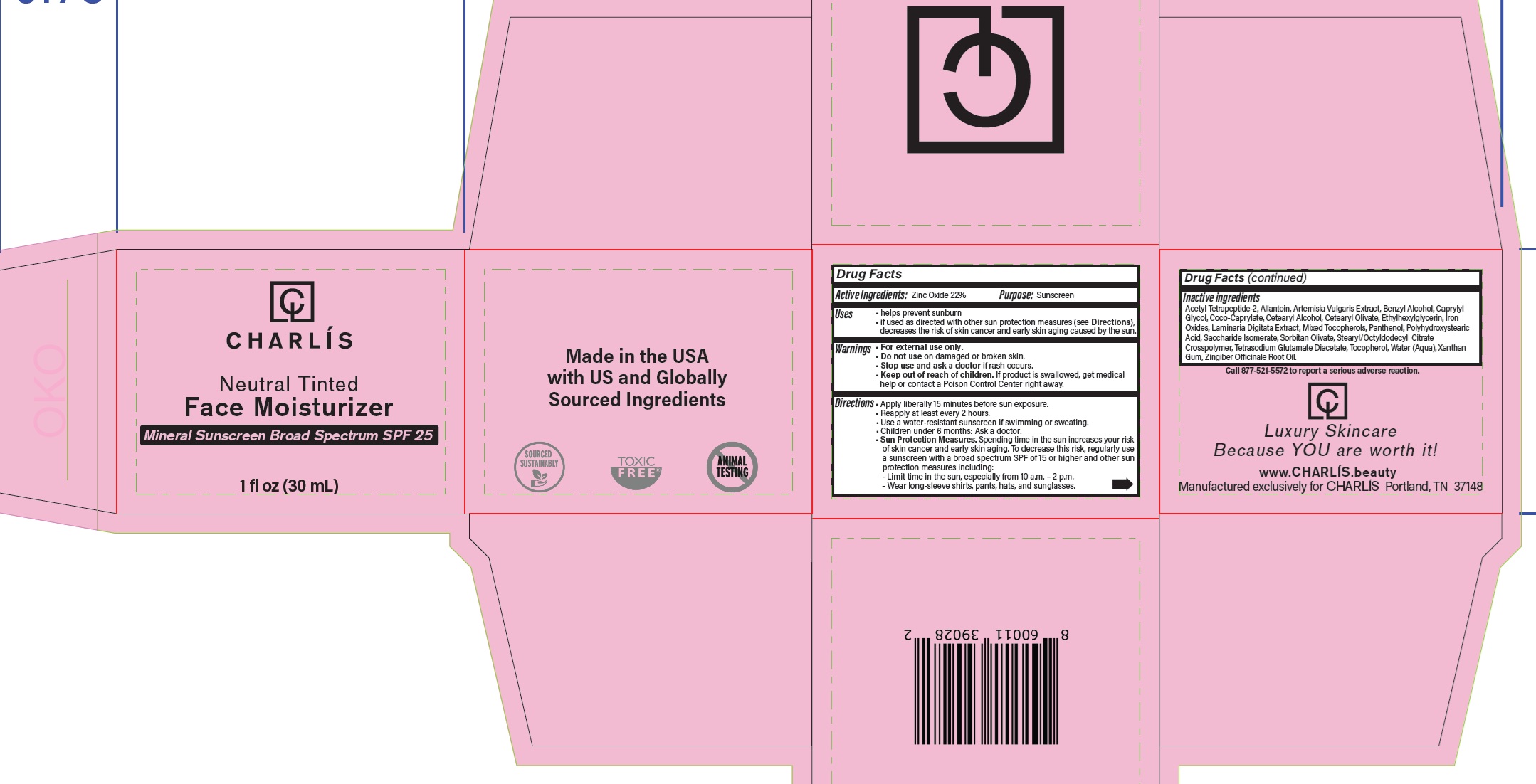 DRUG LABEL: Charlis Neutral Tinted Face Moisturizer Mineral Sunscreen SPF 25
NDC: 85566-322 | Form: CREAM
Manufacturer: CHARLIS LLC
Category: otc | Type: HUMAN OTC DRUG LABEL
Date: 20250418

ACTIVE INGREDIENTS: ZINC OXIDE 220 mg/1 mL
INACTIVE INGREDIENTS: ACETYL TETRAPEPTIDE-2; ALLANTOIN; ARTEMISIA VULGARIS ROOT; BENZYL ALCOHOL; CAPRYLYL GLYCOL; COCO-CAPRYLATE; CETEARYL ALCOHOL; CETEARYL OLIVATE; ETHYLHEXYLGLYCERIN; FERRIC OXIDE RED; LAMINARIA DIGITATA; PANTHENOL; SACCHARIDE ISOMERATE; SORBITAN OLIVATE; STEARYL/OCTYLDODECYL CITRATE CROSSPOLYMER; TETRASODIUM GLUTAMATE DIACETATE; TOCOPHEROL; WATER; XANTHAN GUM

Neutral Tinted Face Moisturizer Mineral Sunscreen SPF 25

Active Ingredients:

Zinc Oxide 22%

Purpose:

Sunscreen

Uses

• helps prevent sunburn
• if used as directed with other sun protection measures (see Directions), decreases the risk of skin cancer and early skin aging caused by the sun.

Warnings

• For external use only.

Do not use

• on damaged or broken skin.

Stop use and ask a doctor

• if rash occurs.

Keep out of reach of children.

• If product is swallowed, get medical help or contact a Poison Control Center right away.

Directions

• Apply liberally 15 minutes before sun exposure.
• Reapply at least every 2 hours.
• Use a water-resistant sunscreen if swimming or sweating.
• Sun Protection Measures.Spending time in the sun increases your riskof skin cancer and early skin aging. To decrease this risk, regularly usea sunscreen with a broad spectrum SPF of 15 or higher and other sun protection measures including:
- Limit time in the sun, especially from 10 a.m. – 2 p.m.
- Wear long-sleeve shirts, pants, hats, and sunglasses.

Inactive ingredients

Acetyl Tetrapeptide-2, Allantoin, Artemisia Vulgaris Extract, Benzyl Alcohol, Caprylyl Glycol, Coco-Caprylate, Cetearyl Alcohol, Cetearyl Olivate, Ethylhexylglycerin, Iron Oxides, Laminaria Digitata Extract, Mixed Tocopherols, Panthenol, Polyhydroxystearic Acid, Saccharide Isomerate, Sorbitan Olivate, Stearyl/Octyldodecyl Citrate Crosspolymer, Tetrasodium Glutamate Diacetate, Tocopherol, Water (Aqua), Xanthan Gum, Zingiber Officinale Root Oil.